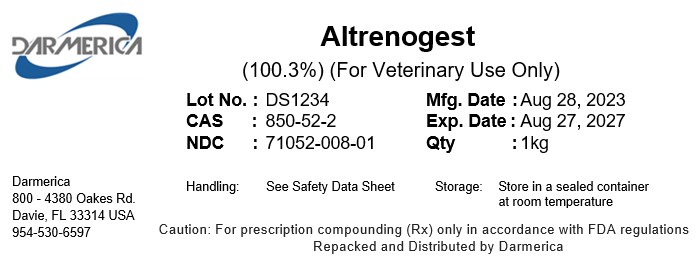 DRUG LABEL: Altrenogest
NDC: 71052-008 | Form: POWDER
Manufacturer: DARMERICA, LLC
Category: other | Type: BULK INGREDIENT - ANIMAL DRUG
Date: 20241219

ACTIVE INGREDIENTS: Altrenogest 1 kg/1 kg

Altrenogest